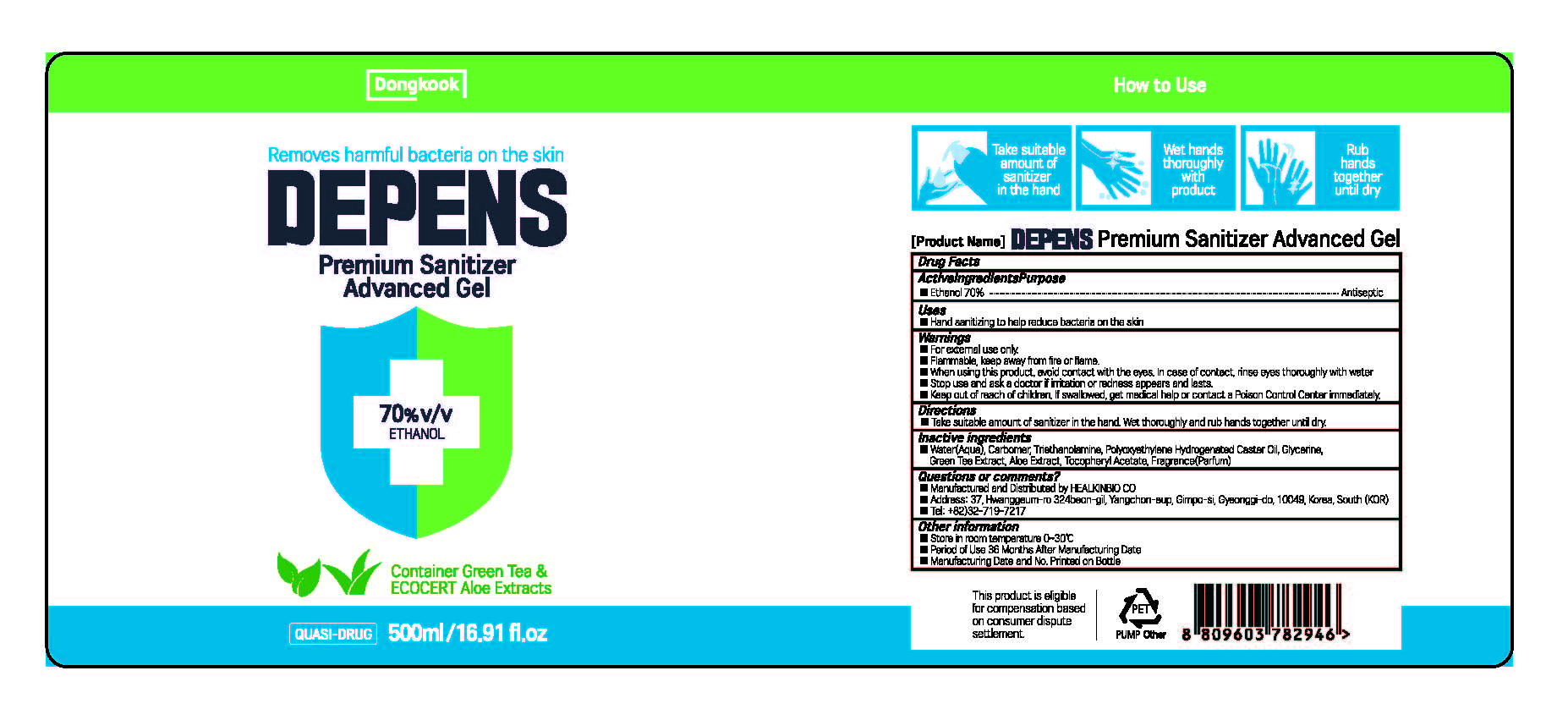 DRUG LABEL: DEPENS PREMIUM SANITIZER
NDC: 76586-002 | Form: Gel
Manufacturer: HEALKINBIO CO.
Category: otc | Type: HUMAN OTC DRUG LABEL
Date: 20210115

ACTIVE INGREDIENTS: alcohol 70 mL/100 mL
INACTIVE INGREDIENTS: Water; glycerin

Active Ingredient(s)

Ethanol 70%

Purpose

Purpose: Antiseptic

Use

 Hand sanitizing to help reduce bacteria on the skin

Warnings

 For external use only.
 Flammable, keep away from fire or flame.
 When using this product, avoid contact with the eyes. In case of contact, rinse eyes thoroughly with water.
 Stop use and ask a doctor if irritation or redness appears and lasts.

 Keep out of reach of children. If swallowed, get medical help or contact a Poison Control Center immediately.

Directions

 Take suitable amount of sanitizer in the hand. Wet thoroughly and rub hands together until dry

Other information

 Store in room temperature 0~30℃

 Period of Use: 36 Months after manufacturing date

 Manufacturing Date and No. Printed on bottle

Inactive ingredients

Water(Aqua), Carbomer, Triethanolamine, Polyoxyethylene Hydrogenated Caster Oil, Glycerin, Green Tea Extract, Aloe Extract, Tocopheryl Acetate, Fragrance(Parfum)